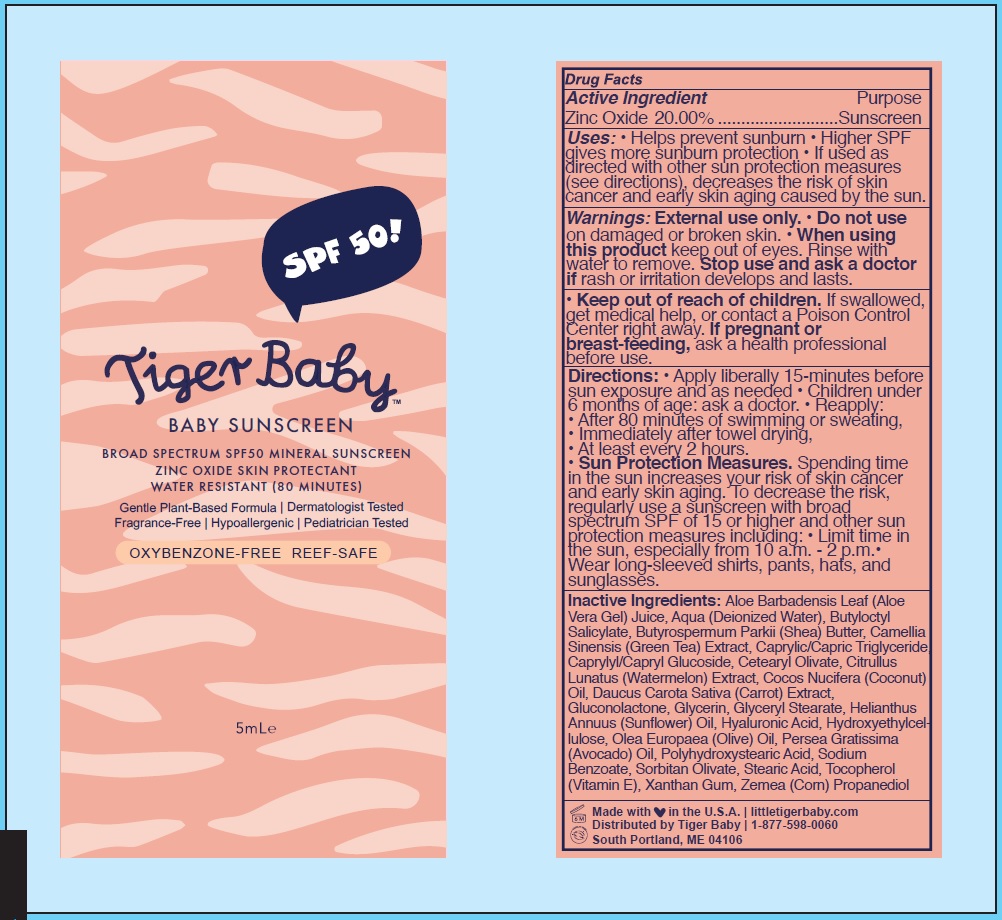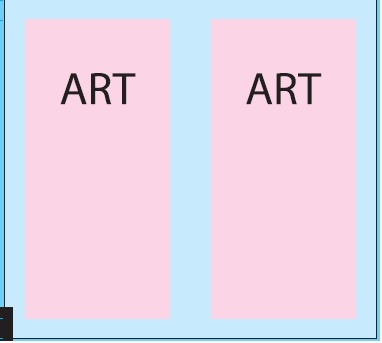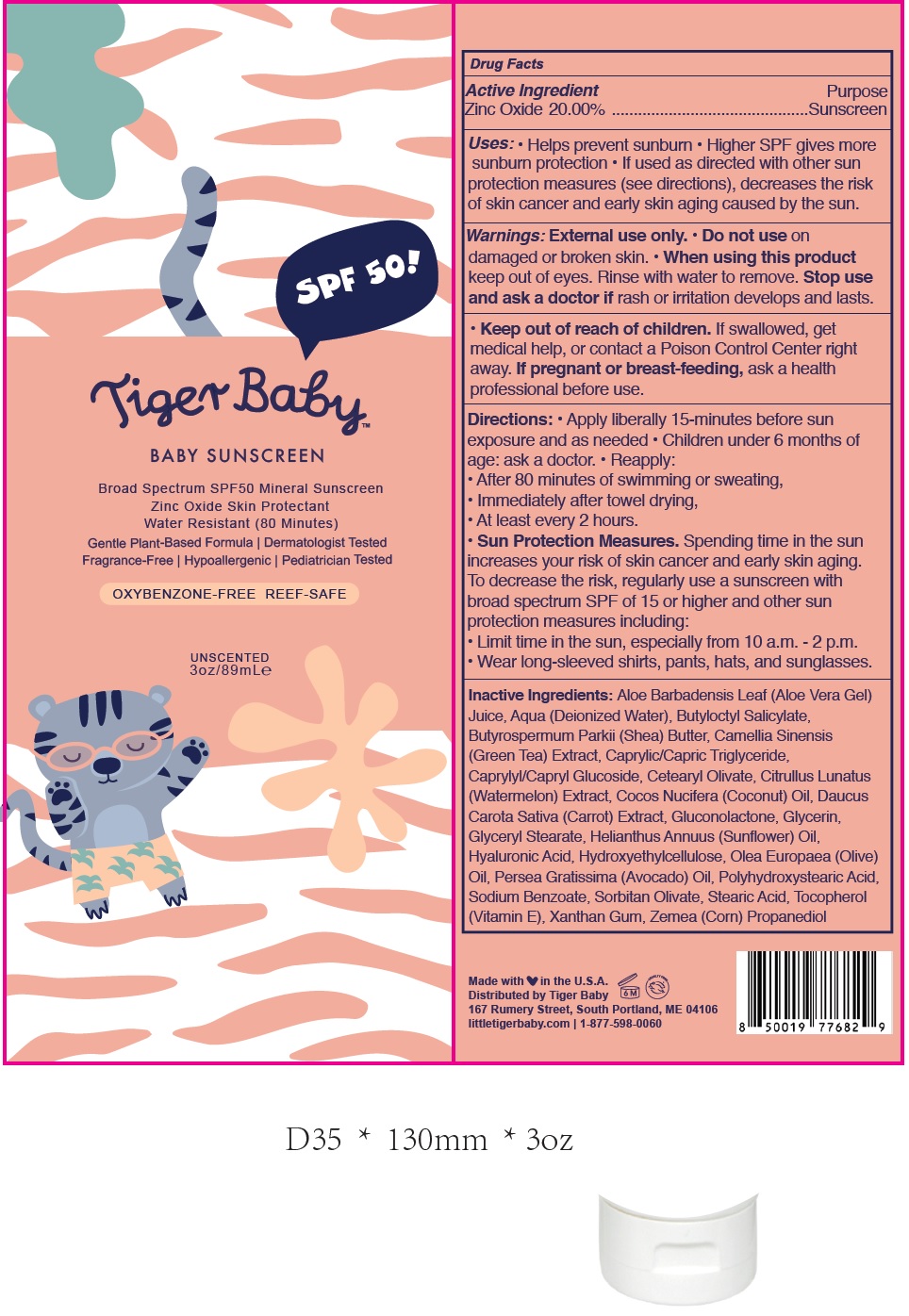 DRUG LABEL: TIGER BABY Baby Sunscreen SPF-50
NDC: 82247-278 | Form: CREAM
Manufacturer: BRICKELL BRANDS LLC
Category: otc | Type: HUMAN OTC DRUG LABEL
Date: 20231111

ACTIVE INGREDIENTS: ZINC OXIDE 200 mg/1 mL
INACTIVE INGREDIENTS: ALOE VERA LEAF; WATER; BUTYLOCTYL SALICYLATE; SHEA BUTTER; GREEN TEA LEAF; MEDIUM-CHAIN TRIGLYCERIDES; CAPRYLYL/CAPRYL OLIGOGLUCOSIDE; CETEARYL OLIVATE; WATERMELON; COCONUT OIL; CARROT; GLUCONOLACTONE; GLYCERIN; GLYCERYL MONOSTEARATE; HELIANTHUS ANNUUS FLOWERING TOP; HYALURONIC ACID; HYDROXYETHYL CELLULOSE, UNSPECIFIED; OLIVE OIL; AVOCADO OIL; SODIUM BENZOATE; SORBITAN OLIVATE; STEARIC ACID; TOCOPHEROL; .ALPHA.-TOCOPHEROL; XANTHAN GUM; CORN

TIGER BABY: Baby Sunscreen SPF-50

Active Ingredient

Zinc Oxide 20.00%

Purpose

Sunscreen

Uses:

• Helps prevent sunburn • Higher SPF gives more sunburn protection • If used as directed with other sun protection measures (see directions), decreases the risk of skin cancer and early skin aging caused by the sun.

Warnings:

External use only.

Do not use

- on damaged or broken skin.

When using this product

- keep out of eyes. Rinse with water to remove.

Stop use and ask a doctor if

rash or irritation develops and lasts.

Keep out of reach of children.

- If swallowed, get medical help, or contact a Poison Control Center right away.

If pregnant or breast-feeding,

ask a health professional before use.

Directions:

• Apply liberally 15-minutes before sun exposure and as needed • Children under 6 months of age: ask a doctor. • Reapply:

• After 80 minutes of swimming or sweating,

• Immediately after towel drying.

• At least every 2 hours.

• Spending time in the sun increases your risk of skin cancer and early skin aging. To decrease the risk, regularly use a sunscreen with broad spectrum SPF of 15 or higher and other sun protection measures including: • Limit time in the sun, especially from 10 a.m. - 2 p.m. • Wear long-sleeved shirts, pants, hats, and sunglasses. Sun Protection Measures.

Inactive Ingredients:

Aloe Barbadensis Leaf (Aloe Vera Gel) Juice, Aqua (Deionized Water), Butyloctyl Salicylate, Butyrospermum Parkii (Shea) Butter, Camellia Sinensis (Green Tea) Extract, Caprylic/Capric Triglyceride, Caprylyl/Capryl Glucoside, Cetearyl Olivate, Citrullus Lunatus (Watermelon) Extract, Cocos Nucifera (Coconut) Oil, Daucus Carota Sativa (Carrot) Extract, Gluconolactone, Glycerin, Glyceryl Stearate, Helianthus Annuus (Sunflower) Oil, Hyaluronic Acid, Hydroxyethylcellulose, Olea Europaea (Olive) Oil, Persea Gratissima (Avocado) Oil, Polyhydroxystearic Acid, Sodium Benzoate, Sorbitan Olivate, Stearic Acid, Tocopherol (Vitamin E), Xanthan Gum, Zemea (Corn) Propanediol